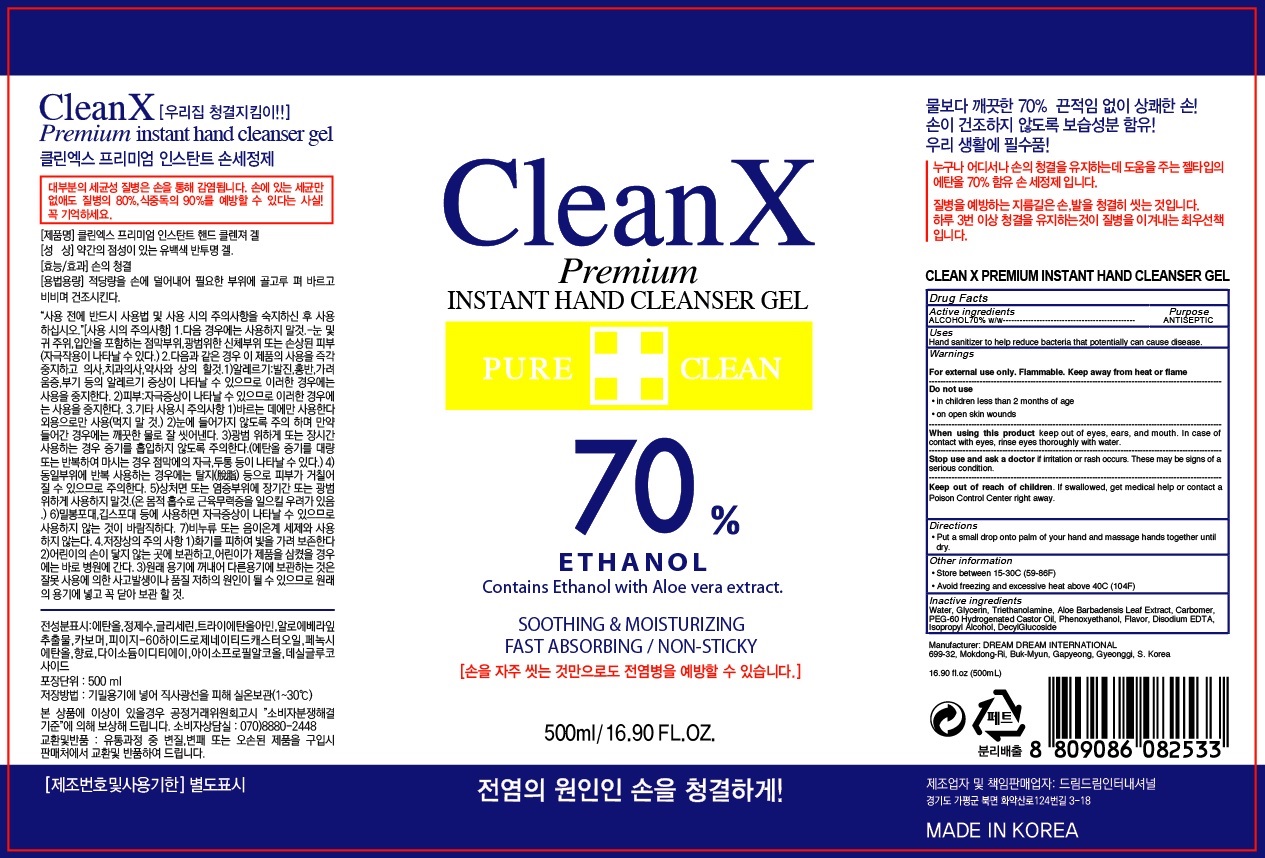 DRUG LABEL: Clean X Premium Instant Hand Cleanser
NDC: 76682-010 | Form: GEL
Manufacturer: DreamDream international
Category: otc | Type: HUMAN OTC DRUG LABEL
Date: 20200501

ACTIVE INGREDIENTS: ALCOHOL 350 mL/500 mL
INACTIVE INGREDIENTS: Water; Glycerin; TROLAMINE; ALOE VERA LEAF; CARBOMER HOMOPOLYMER, UNSPECIFIED TYPE; PEG-60 Hydrogenated Castor Oil; Phenoxyethanol; EDETATE DISODIUM ANHYDROUS; Isopropyl Alcohol; Decyl Glucoside

ACTIVE INGREDIENT

Active ingredient: ALCOHOL 70% w/w

INACTIVE INGREDIENT

Inactive ingredients:

Water, Glycerin, Triethanolamine, Aloe Barbadensis Leaf Extract, Carbomer, PEG-60 Hydrogenated Castor Oil, Phenoxyethanol, Flavor, Disodium EDTA, Isopropyl Alcohol, Decyl Glucoside

PURPOSE

Purpose: ANTISEPTIC

WARNINGS

For external use only. Flammable. Keep away from heat or flame
--------------------------------------------------------------------------------------------------------
Do not use
• in children less than 2 months of age
• on open skin wounds
--------------------------------------------------------------------------------------------------------
When using this product keep out of eyes, ears, and mouth. In case of contact with eyes, rinse eyes thoroughly with water.
--------------------------------------------------------------------------------------------------------
Stop use and ask a doctor if irritation or rash occurs. These may be signs of a serious condition.

KEEP OUT OF REACH OF CHILDREN

If swallowed, get medical help or contact a Poison Control Center right away.

Uses

Hand sanitizer to help reduce bacteria that potentially can cause disease.

Directions

• Put a small drop onto palm of your hand and massage hands together until dry.

Other information

• Store between 15-30C (59-86F)
• Avoid freezing and excessive heat above 40C (104F)